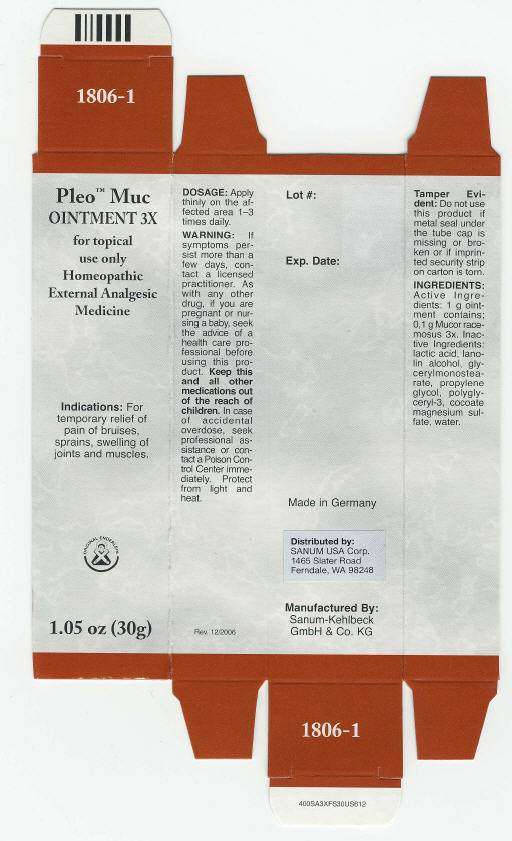 DRUG LABEL: Pleo Muc
NDC: 60681-1806 | Form: OINTMENT
Manufacturer: Sanum Kehlbeck GmbH & Co. KG
Category: homeopathic | Type: HUMAN OTC DRUG LABEL
Date: 20091110

ACTIVE INGREDIENTS: mucor racemosus 3 [hp_X]/30 g
INACTIVE INGREDIENTS: glyceryl monostearate; lactic acid; propylene glycol; water

Pleo™ Muc
OINTMENT 3X

for topical use only
Homeopathic External Analgesic Medicine

1.05 oz (30g)

Indications

For temporary relief of pain of bruises, sprains, swelling of joints and muscles.

DOSAGE

Apply thinly on the affected area 1–3 times daily.

WARNING

If symptoms persist more than a few days, contact a licensed practitioner. As with any other drug, if you are pregnant or nursing a baby, seek the advice of a health care professional before using this product.

KEEP OUT OF REACH OF CHILDREN

Keep this and all other medications out of the reach of children. In case of accidental overdose, seek professional assistance or contact a Poison Control Center immediately.

STORAGE AND HANDLING

Protect from light and heat.

Tamper Evident

Do not use this product if metal seal under the tube cap is missing or broken or if imprinted security strip on carton is torn.

INGREDIENTS

Active Ingredients

1 g ointment contains; 0.1 g Mucor racemosus 3x.

Inactive Ingredients

lactic acid, lanolin alcohol, glycerylmonostearate, propylene glycol, polyglyceryl-3, cocoate magnesium sulfate, water.

Made in Germany

Distributed by:
SANUM USA Corp.
1465 Slater Road
Ferndale, WA 98248

Manufactured By:
Sanum-Kehlbeck
GmbH & Co. KG

Rev. 12/2006

PRINCIPAL DISPLAY PANEL - 30 g Ointment Carton

Pleo™ Muc
OINTMENT 3X

for topical
use only
Homeopathic
External Analgesic
Medicine

Indications: For
temporary relief of
pain of bruises,
sprains, swelling of
joints and muscles.

ORIGINAL ENDERLEIN

1.05 oz (30g)